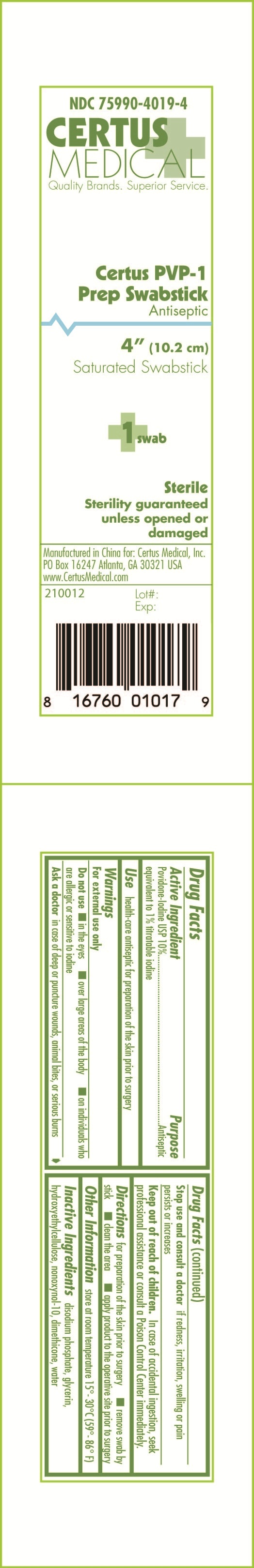 DRUG LABEL: Certus PVP-1 Prep Swabstick
NDC: 75990-4019 | Form: SWAB
Manufacturer: Certus Medical, Inc.
Category: otc | Type: HUMAN OTC DRUG LABEL
Date: 20110408

ACTIVE INGREDIENTS: POVIDONE-IODINE 0.1 mL/1 mL
INACTIVE INGREDIENTS: WATER; GLYCERIN; SODIUM PHOSPHATE, DIBASIC; NONOXYNOL-10; DIMETHICONE; HYDROXYETHYL CELLULOSE (2000 CPS AT 1%)

Certus PVP-1 Prep Swabstick 210012 Drug Facts and Label

Drug Facts Box OTC Active Ingredient Section

Povidone Iodine USP 10%

equivalent to 1% titratable iodine

Drug Facts Box OTC Purpose Section

Antiseptic

Drug Facts Box OTC Indications & Usage Section

health-care antiseptic for preparation of the skin prior to surgery

Drug Facts Box OTC Warnings Section

for external use only

Drug Facts Box OTC Do Not Use Section

in the eyes

over large areas of the body

on individuals who are allergic or sensitive to iodine

Drug Facts Box OTC Ask Doctor Section

in case of deep or puncture wounds, animal bites, or serious burns

Drug Facts Box OTC Stop Use Section

and consult a doctor if redness, irritation, swelling, or pain persists or increases

Drug Facts Box OTC Keep Out of Reach of Children Section

in case of accidental ingestion, seek professional assistance or consult a Poison Control Center immediately

Drug Facts Box OTC Dosage & Administration Section

for preparation of the skin prior to surgery

remove swab by stick

clean the area

apply product to the operative site prior to surgery

Drug Facts Box OTC General Precautions Section

store at room temperature 15^0 - 30^0 C (59^0 - 86^0 F)

Drug Facts Box OTC Inactive Ingredient Section

disodium phosphate, glycerin, hydroxyethylcellulose, nonoxynol-10, dimethicone, water

Certus PVP-1 Prep Swabstick 210012 pouch

210012.jpg Certus PVP-1 Prep Swabstick pouch